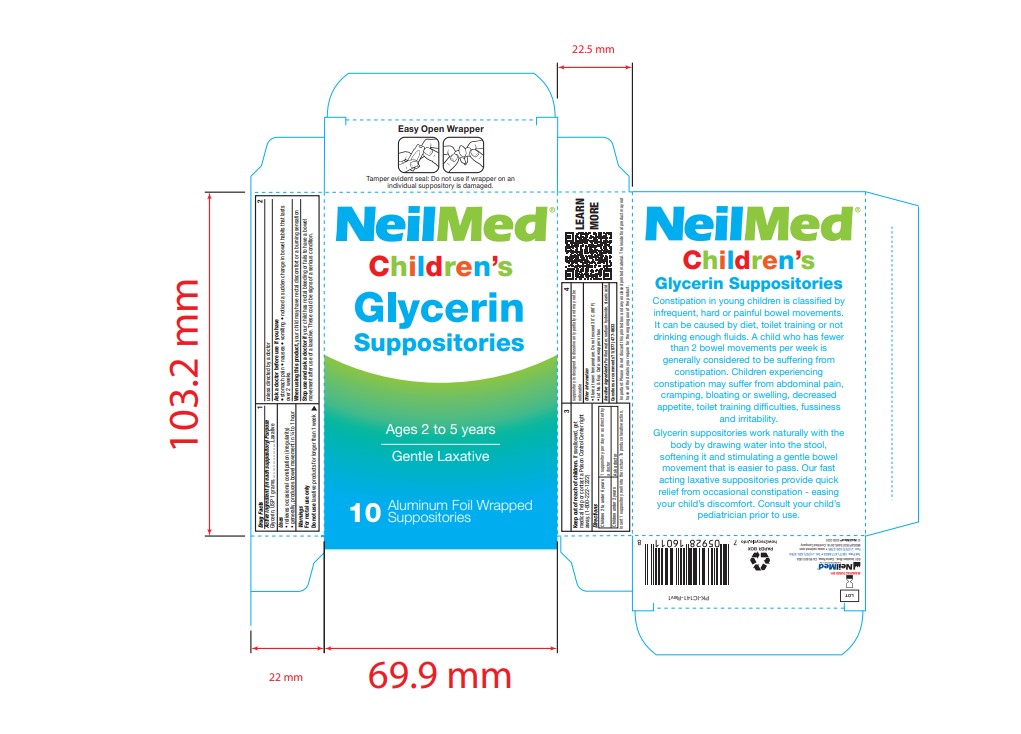 DRUG LABEL: Glycerin
NDC: 13709-333 | Form: SUPPOSITORY
Manufacturer: Neilmed Pharmaceuticals Inc.
Category: otc | Type: HUMAN OTC DRUG LABEL
Date: 20250611

ACTIVE INGREDIENTS: GLYCERIN 1 g/1.25 g
INACTIVE INGREDIENTS: SODIUM HYDROXIDE; WATER; STEARIC ACID

Children's Glycerin Suppositories

Active Ingredient(in each suppository)

Glycerin, USP 1 grams

Purpose

Laxative

Uses

• relieves occasional constipation (irregularity)

• generally, produces bowel movement in ¼ to 1 hour

Warnings

For rectal use only

Do not use

laxative products for longer than 1 week unless directed by a doctor

Ask a doctor before use if you have

• stomach pain • nausea • vomiting • noticed a sudden change in bowel habits that lasts over 2 weeks

When using this product,

your child may have rectal discomfort or a burning sensation

Stop use and ask a doctor if

your child has rectal bleeding or fails to have a bowel movement after use of a laxative. These could be signs of a serious condition.

Keep out of reach of children.

If swallowed, get medical help or contact a Poison Control Center right away. (1-800-222-1222)

Directions

Children 2 to under 6 years | 1 suppository per day or as directed by a doctor
Children under 2 years | Ask a doctor

Insert 1 suppository well into the rectum. To produce laxative action, suppository is designed to dissolve only partially and may not be noticeable

Other information

• Store at room temperature. Do not exceed 30˚ C (86˚ F)

• Lot No. & Exp. Date: see wrapper or box

INACTIVE INGREDIENT

Purified water, sodium hydroxide, stearic acid

Questions or comments?

1(877) 477-8633

Important:

Please do not discard this printed box and any enclosed printed material. The inside final product may not have all the details you require for the ongoing use of the product.